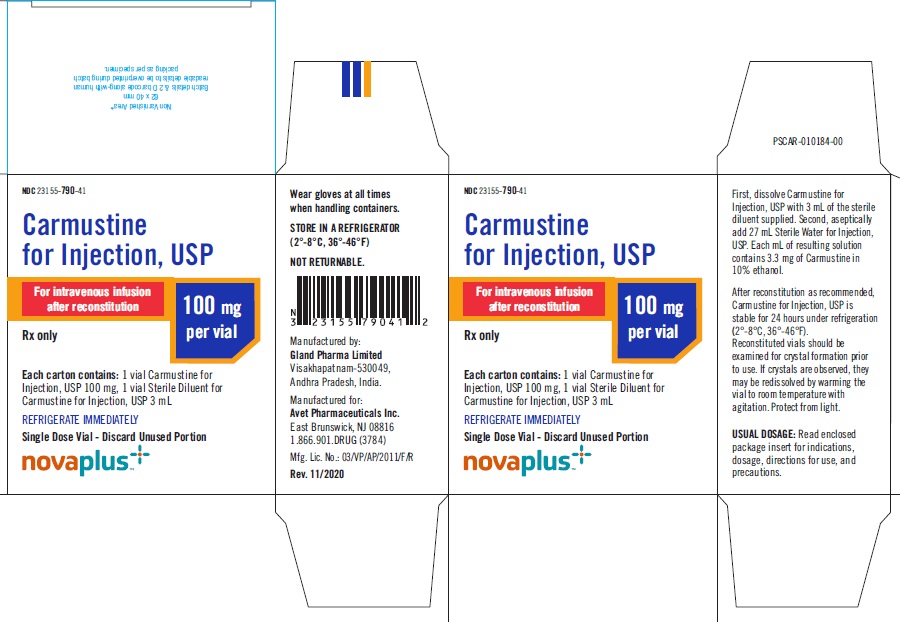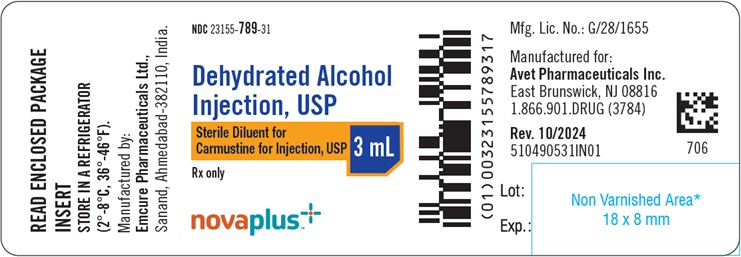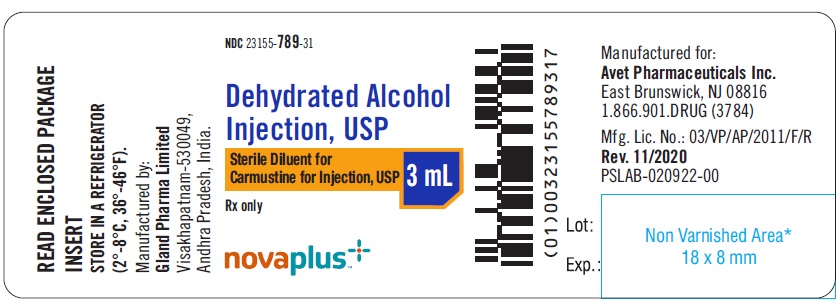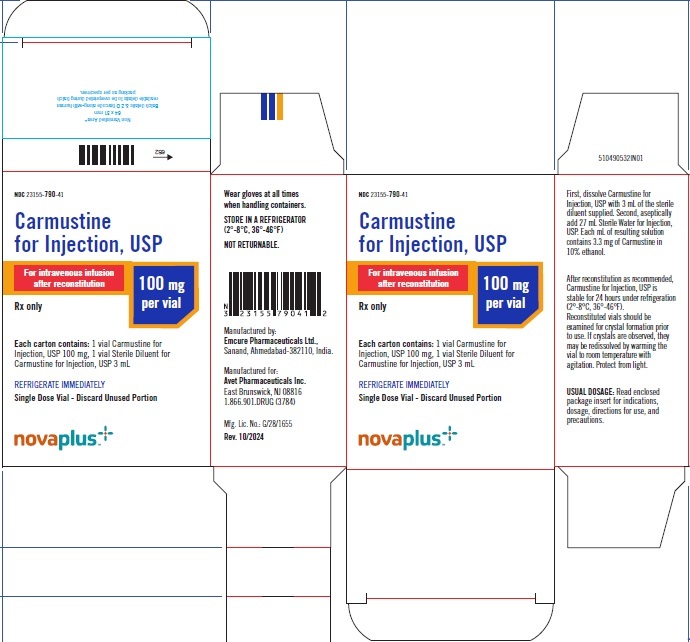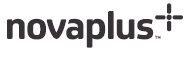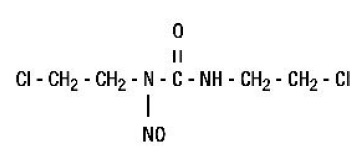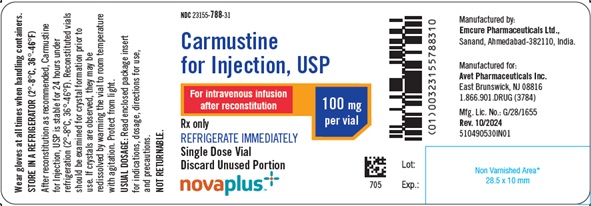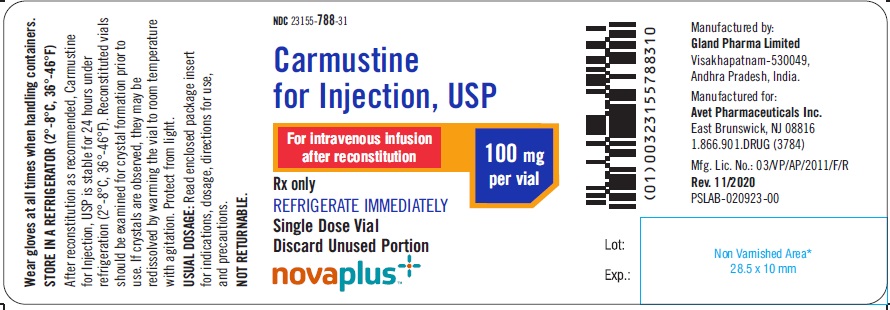 DRUG LABEL: CARMUSTINE
								
NDC: 23155-790 | Form: KIT | Route: INTRAVENOUS
Manufacturer: Heritage Pharmaceuticals Inc. d/b/a Avet Pharmaceuticals Inc.
Category: prescription | Type: HUMAN PRESCRIPTION DRUG LABEL
Date: 20250206

ACTIVE INGREDIENTS: CARMUSTINE 100 mg/30 mL
INACTIVE INGREDIENTS: ALCOHOL

HIGHLIGHTS OF PRESCRIBING INFORMATION

These highlights do not include all the information needed to use CARMUSTINE FOR INJECTION, USP safely and effectively. See full prescribing information for CARMUSTINE FOR INJECTION, USP.
CARMUSTINE for injection, USP for intravenous use
Initial U.S. Approval: 1977

WARNING: MYELOSUPPRESSION and PULMONARY TOXICITY

See full prescribing information for complete boxed warning

• Suppression of marrow function, notably thrombocytopenia and leukopenia, is the most common and severe of the toxic effects of Carmustine for Injection. Monitor blood counts. (5, 6).

• Pulmonary toxicity from Carmustine for Injection appears to be dose related. Patients receiving greater than 1400 mg/m^2 cumulative dose are at significantly higher risk than those receiving less (5, 6).

1 INDICATIONS AND USAGE

Carmustine for Injection, USP is a nitrosourea indicated as palliative therapy as a single agent or in established combination therapy with other approved chemotherapeutic agents in the following:

- Brain tumors glioblastoma, brainstem glioma, medulloblastoma, astrocytoma, ependymoma, and metastatic brain tumors (1)
- Multiple myeloma-in combination with prednisone (1)
- Relapsed or refractory Hodgkin's lymphoma in combination with other approved drugs (1)
- Relapsed or refractory Non-Hodgkin's lymphomas in combination with other approved drugs (1)

2 DOSAGE AND ADMINISTRATION

- Recommended Dosage: As a single agent, 150 to 200 mg/m^2Carmustine for Injection intravenously every 6 weeks as a single dose or divided into daily injections such as 75 to 100 mg/m^2on 2 successive days. Adjust dose for combination therapy or in patients with reduced bone marrow reserve (2.1)
- Administer reconstituted solution only as a slow intravenous infusion over at least 2 hours. (2.2)

3 DOSAGE FORMS AND STRENGTHS

For injection: 100 mg of carmustine lyophilized powder in a single-dose vial for reconstitution and a vial containing 3mL sterile diluent (Dehydrated Alcohol Injection, USP)

4 CONTRAINDICATIONS

- Hypersensitivity (4)

5 WARNINGS AND PRECAUTIONS

- Administration Reactions: Extravasation may occur; monitor infusion site closely during administration (5.3)
- Carcinogenicity: Potentially carcinogenic to humans. Monitor patient periodically for such signs and apprise the patient of the symptoms for which they need to seek medical help. (5.4)
- Ocular Toxicity: Has occurred when administered via unapproved intraarterial intracarotid route. (5.5)
- Embryo-Fetal toxicity: Can cause fetal harm. Advise females of reproductive potential of the potential risk to a fetus and to avoid pregnancy. (5.6)

6 ADVERSE REACTIONS

Most common adverse reactions (>1%) are nausea, vomiting, renal toxicity, pneumonitis, pulmonary toxicity, myelosuppression (6)

To report SUSPECTED ADVERSE REACTIONS, contact Avet Pharmaceuticals Inc. at 1-866-901-DRUG (3784) or FDA at 1-800-FDA-1088 or www.fda.gov/medwatch.

7 DRUG INTERACTIONS

- Cimetidine: Increased myelosuppression with concomitant use. (7.1)
- Phenobarbital: Induces carmustine metabolism, reducing exposure. May lead to reduced efficacy. (7.1)
- Phenytoin: Carmustine for Injection may reduce the efficacy of phenytoin. (7.2)

8 USE IN SPECIFIC POPULATIONS

- Lactation: Advise lactating females not to breastfeed (8.2)

FULL PRESCRIBING INFORMATION

WARNING: MYELOSUPPRESSION and PULMONARY TOXICITY

Myelosuppression

Carmustine for Injection, USP causes suppression of marrow function (including thrombocytopenia and leukopenia), which may contribute to bleeding and overwhelming infections, [see Warnings and Precautions (5.1) and Adverse Reactions (6)]. Monitor blood counts weekly for at least 6 weeks after each dose. Adjust dosage based on nadir blood counts from the prior dose [see Dosage and Administration (2.1)]. Do not administer a repeat course of Carmustine for Injection until blood counts recover.

Pulmonary Toxicity

Carmustine for Injection causes dose-related pulmonary toxicity. Patients receiving greater than 1400 mg/m^2 cumulative dose are at significantly higher risk than those receiving less. Delayed pulmonary toxicity can occur years after treatment, and can result in death, particularly in patients treated in childhood [see Adverse Reactions (6) and Use in Specific Populations (8.4)].

1 INDICATIONS AND USAGE

Carmustine for Injection, USP is indicated as palliative therapy as a single agent or in established combination therapy in the following:

- Brain tumors glioblastoma, brainstem glioma, medulloblastoma, astrocytoma, ependymoma, and metastatic brain tumors.
- Multiple myeloma in combination with prednisone.
- Relapsed or refractory Hodgkin's lymphoma in combination with other approved drugs.
- Relapsed or refractory Non-Hodgkin's lymphomas in combination with other approved drugs.

2 DOSAGE AND ADMINISTRATION

2.1 Dosage

The recommended dose of Carmustine for Injection, USP as a single agent in previously untreated patients is 150 to 200 mg/m^2 intravenously every 6 weeks. Administer as a single dose or divided into daily injections such as 75 to 100 mg/m^2 on two successive days. Lower the dose when Carmustine for Injection is used with other myelosuppressive drugs or in patients in whom bone marrow reserve is depleted. Administer Carmustine for Injection for the duration according to the established regimen. Premedicate each dose with anti-emetics.

Adjust doses subsequent to the initial dose according to the hematologic response of the patient to the preceding dose. The following schedule is suggested as a guide to dosage adjustment:

Nadir After Prior Dose |  | Percentage of Prior Dose to be Given
Leukocytes/mm^3 | Platelets/mm^3
>4000 | >100,000 | 100%
3000-3999 | 75,000-99,999 | 100%
2000-2999 | 25,000-74,999 | 70%
<2000 | <25,000 | 50%

The hematologic toxicity can be delayed and cumulative. Monitor blood counts weekly. Do not administer a repeat course of Carmustine for Injection, USP until circulating blood elements have returned to acceptable levels (platelets above 100 Gi/L, leukocytes above 4 Gi/L and absolute neutrophil count above 1 Gi/L). The usual interval between courses is 6 weeks.

Evaluate renal function prior to administration and periodically during treatment. For patients with compromised renal function, monitor for toxicity more frequently. Discontinue Carmustine for Injection, USP if the creatinine clearance is less than 10 mL/min. Do not administer Carmustine for Injection, USP to patients with compromised renal function. Monitor transaminases and bilirubin periodically during treatment. [see Adverse Reactions (6)].

2.2 Preparation and Administration of Intravenous Solution

- Dissolve Carmustine for Injection, USP with 3 mL of the supplied sterile diluent (Dehydrated Alcohol Injection, USP).
- Aseptically add 27 mL Sterile Water for Injection, USP.
  - Each mL of resulting solution contains 3.3 mg of Carmustine for Injection in 10% ethanol. Such solutions should be protected from light.
  - The reconstituted solution is a clear, colorless to yellowish solution.
- Once reconstituted, the solution must be further diluted with Sodium Chloride Injection, USP or 5% Dextrose Injection, USP.
  - Examine reconstituted vials for crystal formation prior to use. If crystals are observed, they may be re-dissolved by warming the vial to room temperature with agitation.
  - Parenteral drug products should be inspected visually for particulate matter and discoloration prior to administration, whenever solution and container permit.
  - After reconstitution as recommended, Carmustine for Injection is stable for 24 hours under refrigeration (2°-8°C, 36°-46°F) in glass container. Examine reconstituted vials for crystal formation prior to use. If crystals are observed, they may be redissolved by warming the vial to room temperature with agitation.
  - Vials reconstituted as directed and further diluted with 500 mL Sodium Chloride Injection, USP or 5% Dextrose Injection, USP, in glass or polypropylene containers to a concentration of 0.2 mg/mL, should be stored at room temperature, protected from light and utilized within 8 hours. These solutions are also stable 24 hours under refrigeration (2°-8°C, 36°-46°F) and an additional 6 hours at room temperature protected from light.
- Administer reconstituted solution by slow intravenous infusion over at least two hours. Administration of Carmustine for Injection over a period of less than two hours can lead to pain and burning at the site of injection. Monitor the injected area during the administration. The rate of administration of the intravenous infusion should not be more than 1.66 mg/m^2/min.
- See Section 16.2 for important instructions on the storage and handling of the injection. Carmustine for Injection is a cytotoxic drug. Follow applicable special handling and disposal procedures.^1
- The lyophilized dosage formulation contains no preservatives and is not intended for use as a multiple dose vial. Discard unused portion.

Accidental contact of reconstituted Carmustine for Injection, USP with the skin has caused transient hyperpigmentation of the affected areas. Wear impervious gloves to minimize the risk of dermal exposure impervious gloves when handling vials containing Carmustine for Injection. Immediately wash the skin or mucosa thoroughly with soap and water if Carmustine for Injection lyophilized material or solution contacts the skin or mucosa^1.

3 DOSAGE FORMS AND STRENGTHS

For injection: 100 mg of carmustine as a lyophilized powder in a single-dose vial for reconstitution and a vial containing 3 mL sterile diluent (Dehydrated Alcohol Injection, USP).

4 CONTRAINDICATIONS

Carmustine for Injection is contraindicated in patients with previous hypersensitivity to Carmustine for Injection or its components.

5 WARNINGS AND PRECAUTIONS

5.1 Myelosuppression

Bone marrow toxicity is a dose-limiting, common and severe toxic effect of Carmustine for Injection occurring 4-6 weeks after drug administration (thrombocytopenia occurs at about 4 weeks post-administration persisting for 1 to 2 weeks; leukopenia occurs at 5 to 6 weeks after a dose of Carmustine for Injection persisting for 1 to 2 weeks; thrombocytopenia is generally more severe than leukopenia; anemia is less frequent and less severe compared to thrombocytopenia and/or leukopenia) Complete blood count should therefore be monitored weekly for at least six weeks after a dose. Repeat doses of Carmustine for Injection should not be given more frequently than every six weeks. The bone marrow toxicity of Carmustine for Injection is cumulative and therefore the dosage adjustment must be considered on the basis of nadir blood counts from prior dose [see Adverse Reactions (6)]. Greater myelotoxicity (e.g., leukopenia and neutropenia) has been reported when carmustine was combined with cimetidine [see Drug Interactions (7)].

5.2 Pulmonary toxicity

Cases of fatal pulmonary toxicity with Carmustine for Injection have been reported. Pulmonary toxicity characterized by pulmonary infiltrates and/or fibrosis has been reported to occur from 9 days to 43 months after treatment with Carmustine for Injection and related nitrosoureas. Pulmonary toxicity from Carmustine for Injection is dose-related. Patients receiving greater than 1400 mg/m^2 cumulative dose are at significantly higher risk than those receiving less. However, there have been reports of pulmonary fibrosis in patients receiving lower total doses. Interstitial fibrosis (with lower doses) occurred rarely. Additionally, delayed onset pulmonary fibrosis occurring up to 17 years after treatment has been reported in patients who received Carmustine for Injection (in cumulative doses ranging from 770 to 1800 mg/m^2 combined with cranial radiotherapy for intracranial tumors) in childhood and early adolescence. Other risk factors include past history of lung disease and duration of treatment. Baseline pulmonary function studies should be conducted along with frequent pulmonary function tests during treatment. Patients with a baseline below 70% of the predicted forced vital capacity (FVC) or carbon monoxide diffusing capacity (DLCO) are particularly at risk.

5.3 Administration Reactions

Injection site reactions may occur during the administration of Carmustine for Injection. Rapid intravenous infusion of Carmustine for Injection may produce intensive flushing of the skin and suffusion of the conjunctiva within 2 hours, lasting about 4 hours. It is also associated with burning at the site of injection although true thrombosis is rare. Given the possibility of extravasation, close monitoring of the infusion site for possible infiltration during drug administration is recommended. A specific treatment for extravasation reactions is unknown at this time.

5.4 Carcinogenicity

Long-term use of nitrosoureas, such as Carmustine for Injection, has been reported to be associated with the development of secondary malignancies. Carmustine was carcinogenic when administered to laboratory animals [see Nonclinical Toxicity (13.1)]. Nitrosourea therapy, such as Carmustine for Injection, has carcinogenic potential in humans. Patients treated with Carmustine for Injection should be monitored long-term for development of second malignancies.

5.5 Ocular Toxicity

Carmustine for Injection has been administered through an intraarterial intracarotid route; this procedure is investigational and has been associated with ocular toxicity. Safety and effectiveness of the intra-arterial route have not been established.

5.6 Embryo-Fetal Toxicity

Carmustine was embryotoxic in rats and rabbits and teratogenic in rats when given in doses lower than the maximum cumulative human dose based on body surface area. There are no adequate and well- controlled studies in pregnant women. Advise pregnant women of the potential risk to the fetus [see Use in Specific Populations (8.1, 8.3)]. Advise females of reproductive potential to use highly effective contraception during and after treatment with Carmustine for Injection for at least 6 months after therapy. Advise males of reproductive potential to use effective contraception during and after treatment with Carmustine for Injection for at least 3 months after therapy [see Use in Specific Populations (8.1, 8.3)].

6 ADVERSE REACTIONS

The following serious adverse reactions are described elsewhere in the labeling:

- Myelosuppression [see Warnings and Precautions (5.1)]
- Pulmonary toxicity [see Warnings and Precautions (5.2)]
- Administration Reactions [see Warnings and Precautions (5.3)]
- Carcinogenicity [see Warnings and Precautions (5.4)]
- Ocular Toxicity [see Warnings and Precautions (5.5)]

The following adverse reactions associated with the use of Carmustine for Injection were identified in clinical studies or postmarketing reports. Because some of these reactions were reported voluntarily from a population of uncertain size, it is not always possible to reliably estimate their frequency or establish a causal relationship to drug exposure.

Cardiac Disorders

Tachycardia and chest pain.

Eye Disorders

Conjunctival edema, conjunctival hemorrhage, blurred vision and loss of depth perception

Gastrointestinal Toxicity

Nausea, vomiting, anorexia, and diarrhea

Hepatotoxicity

Increased transaminase, increased alkaline phosphatase, increased bilirubin levels

Infections and Infestations

Opportunistic infection (including with fatal outcome).

Neoplasms Benign, Malignant and Unspecified (including cysts and polyps)

Acute leukemia, bone marrow dysplasias.

Nephrotoxicity

Progressive azotemia, decrease in kidney size, renal failure

Nervous System Disorders

Headaches, encephalopathy, and seizures

Pulmonary Toxicity

Pneumonitis, interstitial lung disease

Reproductive System and Breast Disorders

Gynecomastia

Skin and Subcutaneous Tissue Disorders

Burning sensation, hyperpigmentation, swelling, pain, erythema, skin necrosis, alopecia, allergic reaction

Vascular Disorders

Veno-occlusive disease.

7 DRUG INTERACTIONS

7.1 Effect of other drugs on Carmustine for Injection

Cimetidine: Greater myelosuppression (e.g., leukopenia and neutropenia) has been reported when oral cimetidine has been coadministered with carmustine. Consider alternative drugs to cimetidine.

Phenobarbital: Phenobarbital induces the metabolism of carmustine and may compromise antitumor activity of Carmustine for Injection. Consider alternative drugs to phenobarbital.

7.2 Effect of Carmustine for Injection on other drugs

Phenytoin: Carmustine for Injection when coadministered with phenytoin may reduce phenytoin serum concentrations. Consider alternative drugs to phenytoin.

8 USE IN SPECIFIC POPULATIONS

8.1 Pregnancy

Risk Summary

Carmustine for Injection can cause fetal harm when administered to a pregnant woman based on the mechanism of action [see Clinical Pharmacology (12.1)] and findings in animals [see Data]. Limited available data with Carmustine for Injection use in pregnant women are insufficient to inform a drug-associated risk of major birth defects and miscarriage. Carmustine was embryotoxic in rats and rabbits and teratogenic in rats (thoracoabdominal closure, neural tube, and eye defects and malformations of the skeletal system of the fetus) when given in doses lower than the maximum cumulative human dose based on body surface area. Consider the benefits and risks of Carmustine for Injection for the mother and possible risks to the fetus when prescribing Carmustine for Injection to a pregnant woman.

Adverse outcomes in pregnancy occur regardless of the health of the mother or the use of medications. The estimated background risk of major birth defects and miscarriage for the indicated population is unknown. In the U.S. general population, the estimated background risk of major birth defects and miscarriage in clinically recognized pregnancies is 2-4% and 15-20%, respectively.

Data

Animal Data

Intraperitoneal (IP) administration of carmustine to pregnant rats 14 days prior to mating and during the period of organogenesis at cumulative doses ≥ 26 mg/kg (158 mg/ m^2), approximately 0.1 times the maximum cumulative human dose of 1400 mg/m^2, resulted in pre-implantation loss, increased resorptions (including completely resorbed litters), and reduced the number of live births in the presence of maternal toxicity.

Carmustine administered IP to pregnant rats during the period of organogenesis at cumulative doses ≥ 4 mg/kg (24 mg/m^2), approximately 0.02 times the maximum cumulative human dose based on a mg/m^2 basis, resulted in reduced fetal weight and various malformations, which included thoracoabdominal closure defects, neural tube defects, and eye defects, including microphthalmia/anophthalmia, and skeletal anomalies in the skull, sternebra, vertebrae and ribs, and reduced skeletal ossification) in the presence of maternal toxicity. Embryo-fetal death was observed at cumulative doses ≥ 8 mg/kg (48 mg/m^2), approximately 0.03 times the maximum cumulative human dose on a mg/ m^2 basis. Intravenous (IV) administration of carmustine to rats at a cumulative dose of 50 mg/kg (300 mg/m^2), approximately 0.2 times the maximum cumulative human dose on a mg/m^2 basis, during the last quarter of pregnancy resulted in the death of offspring within 4 months. Carmustine administered IV to rabbits during the period of organogenesis resulted in spontaneous abortions in mothers and growth defects in the fetus, mainly at cumulative doses ≥ 13 mg/kg (156 mg/ m^2), approximately 0.1 times the maximum cumulative human dose on a mg/ m^2 basis.

8.2 Lactation

Risk Summary

There is no information regarding the presence of carmustine in human milk, the effects on the breastfed infant, or the effects on milk production. Because many drugs are excreted in human milk and because of the potential for serious adverse events (e.g., carcinogenicity and myelosuppression) in nursing infants, nursing should be discontinued while taking Carmustine for Injection.

8.3 Females and Males of Reproductive Potential

Contraception

Advise female patients to avoid pregnancy during treatment with Carmustine for Injection because of the risk of fetal harm [see Use in Specific Populations (8.1)].

Advise female patients of reproductive potential to use highly effective contraception during and for up to six months after completion of treatment.

Advise males with female sexual partners of reproductive potential to use effective contraception during Carmustine for Injection treatment and for at least three months after the final dose of Carmustine for Injection [see Nonclinical Toxicology (13.1)].

Infertility

Based on nonclinical findings, male fertility may be compromised by treatment with Carmustine for Injection [see Nonclinical Toxicology (13.1)].

8.4 Pediatric Use

Safety and effectiveness in children have not been established. Delayed onset pulmonary fibrosis occurring up to 17 years after treatment has been reported in a long-term study of patients who received Carmustine for Injection in childhood and early adolescence (1-16 years). Eight out of the 17 patients (47%) who survived childhood brain tumors, including all the 5 patients initially treated at less than 5 years of age, died of pulmonary fibrosis, [see Adverse Reactions (6.1)].

8.5 Geriatric Use

Clinical studies of Carmustine for Injection did not include sufficient numbers of subjects aged 65 and over to determine whether they respond differently from younger subjects. Other reported clinical experience has not identified differences in responses between the elderly and younger patients. In general, dose selection for an elderly patient should be cautious, usually starting at the low end of the dose range, reflecting the greater frequency of decreased hepatic, renal, or cardiac function, and of concomitant disease or other drug therapy.

Carmustine for Injection and its metabolites are known to be substantially excreted by the kidney, and the risk of toxic reactions to this drug may be greater in patients with impaired renal function. Because elderly patients are more likely to have decreased renal function, care should be taken in dose selection, and renal function should be monitored.

10 OVERDOSAGE

The main result of overdose is myeloablation. No proven antidotes have been established for Carmustine for Injection overdosage.

11 DESCRIPTION

The active ingredient in Carmustine for Injection, USP is a nitrosourea with the chemical name 1,3-bis(2-chloroethyl)-1-nitrosourea and a molecular weight of 214.06. The drug product is supplied as sterile lyophilized pale yellow flakes or a congealed mass, and it is highly soluble in alcohol and lipids, and poorly soluble in water. Carmustine for Injection is administered by intravenous infusion after reconstitution, as recommended.

The structural formula of carmustine is:

Carmustine for Injection is available in 100-mg single dose vials of lyophilized material. Sterile diluent for constitution of Carmustine for Injection is co-packaged with the active drug product for use in constitution of the lyophile. The diluent is supplied in a vial containing 3 mL of Dehydrated Alcohol Injection, USP.

12 CLINICAL PHARMACOLOGY

12.1 Mechanism of Action

The mechanism of action of carmustine is not fully understood. While carmustine alkylates DNA and RNA, it is not cross-resistant with other alkylators. As with other nitrosoureas, it may also inhibit several key enzymatic processes by carbamoylation of amino acids in proteins. The metabolites may contribute to antitumor activity and toxicities of carmustine.

12.2 Pharmacodynamics

The exposure-response relationship for efficacy or safety is unknown.

12.3 Pharmacokinetics

Distribution

Carmustine crosses the blood-brain barrier. Levels of radioactivity in the CSF are greater than or equal to 50% of those measured concurrently in plasma.

Elimination

Following a short intravenous infusion, the reported elimination half-life ranges from 15 minutes to 75 minutes.

Metabolism

Carmustine may be inactivated through denitrosation reactions catalyzed by both cytosolic and microsomal enzymes, including NADPH and glutathione-S-transferase.

Excretion

Approximately 60% to 70% of a total dose is excreted in the urine within 96 hours. Approximately 10% is eliminated as respiratory CO2.

13 NONCLINICAL TOXICOLOGY

13.1 Carcinogenesis, Mutagenesis, Impairment of Fertility

Carmustine is carcinogenic in rats and mice, producing a marked increase in tumor incidence in doses approximating those employed clinically. Nitrosourea therapy does have carcinogenic potential in humans [see Adverse Reactions (6.1)].

Carmustine was mutagenic and clastogenic in multiple in vitro and in vivo genetic toxicology studies.

Male rats treated with carmustine at cumulative doses ≥ 36 mg/kg (216 mg/ m^2), approximately 0.15 times the maximum cumulative human dose on a mg/ m^2 basis, showed decreases in reproductive potential when mated with untreated female rats (e.g., decreased implantations, increased resorption rate, and a decrease in viable fetuses).

15 REFERENCES

1. "OSHA Hazardous Drugs." OSHA. http://www.osha.gov/SLTC/hazardousdrugs/index.html

16 HOW SUPPLIED/STORAGE AND HANDLING

16.1 How Supplied

Carmustine for Injection, USP. Each package includes a vial containing 100 mg carmustine and a vial containing 3 mL sterile diluent.

NDC 23155-790-41

16.2 Storage and Handling

Store product and diluent in a refrigerator (2°-8°C, 36°-46°F).

Stability

Store the unopened vial of the dry drug in a refrigerator (2°-8°C, 36°-46°F). Store the diluent vials in a refrigerator (2°-8°C, 36°-46°F). The recommended storage of unopened Carmustine for Injection vials provides a stable product for up to 3 years.

Compatibility/ Incompatibility with Containers

The intravenous solution is unstable in polyvinyl chloride container. DO NOT USE PVC Containers.

Administer Carmustine for Injection solution from the glass bottles or polypropylene container only. Ensure the polypropylene containers used are PVC free and DEHP free.

Important Note

Carmustine for Injection, USP has a low melting point (30.5°-32.0°C or 86.9°-89.6°F). Exposure of the drug to this temperature or above will cause the drug to liquefy and appear as an oil film on the vials. This is a sign of decomposition and vials should be discarded. If there is a question of adequate refrigeration upon receipt of this product, immediately inspect the vial in each individual carton. Hold the vial to a bright light for inspection. The Carmustine for Injection will appear as a very small amount of dry flakes or dry congealed mass. If this is evident, the Carmustine for Injection is suitable for use and should be refrigerated immediately.

17 PATIENT COUNSELING INFORMATION

Myelosuppression [see Warnings and Precautions (5.1)].

A serious and frequent toxicity of Carmustine for Injection is delayed myelosuppression and usually occurs 4 to 6 weeks after drug administration. Hence, patients should be advised to get blood counts monitored weekly for at least 6 weeks. The bone marrow toxicity of Carmustine for Injection is cumulative.

Pulmonary Toxicity [see Warnings and Precautions (5.2)].

Advise patients to contact a health care professional immediately for any of the following: shortness of breath, particularly during exercise, dry, hacking cough, fast, shallow breathing, gradual unintended weight loss, tiredness, aching joints and muscles, clubbing (widening and rounding) of the tips of the fingers or toes.

Seizures [see Adverse Reactions (6)]

Inform the patient that they may suffer from fits and advise them to get medical attention immediately in such cases.

Pregnancy [see Warnings and Precautions (5.6) and Use in Specific Populations (8.1 and 8.3)]

Advise pregnant women and females of reproductive potential that Carmustine for Injection exposure during pregnancy can result in fetal harm. Advise female patients to contact their healthcare provider with a known or suspected pregnancy. Advise women of reproductive potential to avoid becoming pregnant. Advise females of reproductive potential to use effective contraception during treatment.

Lactation [see Use in Specific Populations (8.2)]

Advise the female patient to discontinue nursing while taking Carmustine for Injection.

Manufactured by:

Gland Pharma Limited

Visakhapatnam-530049,

Andhra Pradesh, India.

or

Manufactured by:

Emcure Pharmaceuticals Ltd.,

Sanand, Ahmedabad-382110, India.

Manufactured for:

Avet Pharmaceuticals Inc.

East Brunswick, NJ 08816

1.866.901.DRUG (3784)

Novaplus is a registered trademark of Vizient, Inc.

Revised: 10/2024

PACKAGE LABEL.PRINCIPAL DISPLAY PANEL - diluent label

NDC 23155-789-31

Rx only

Dehydrated Alcohol Injection, USP

3 mL

Sterile Diluent for Carmustine for Injection, USP

PACKAGE LABEL.PRINCIPAL DISPLAY PANEL - vial label

NDC 23155-788-31

Carmustine for Injection, USP

100 mg per vial

For intravenous infusion after reconstitution

REFRIGERATE IMMEDIATELY

Single Dose Vial - Discard Unused Portion

PACKAGE LABEL.PRINCIPAL DISPLAY PANEL - carton

NDC 23155-790-41 Rx only Carmustine for Injection, USP 100 mg per vial Each carton contains: 1 vial Carmustine for Injection, USP 100 mg, 1 vial Sterile Diluent for Carmustine for Injection, USP 3 mL For intravenous infusion after reconstitution REFRIGERATE IMMEDIATELY Single Dose Vial – Discard Unused Portion